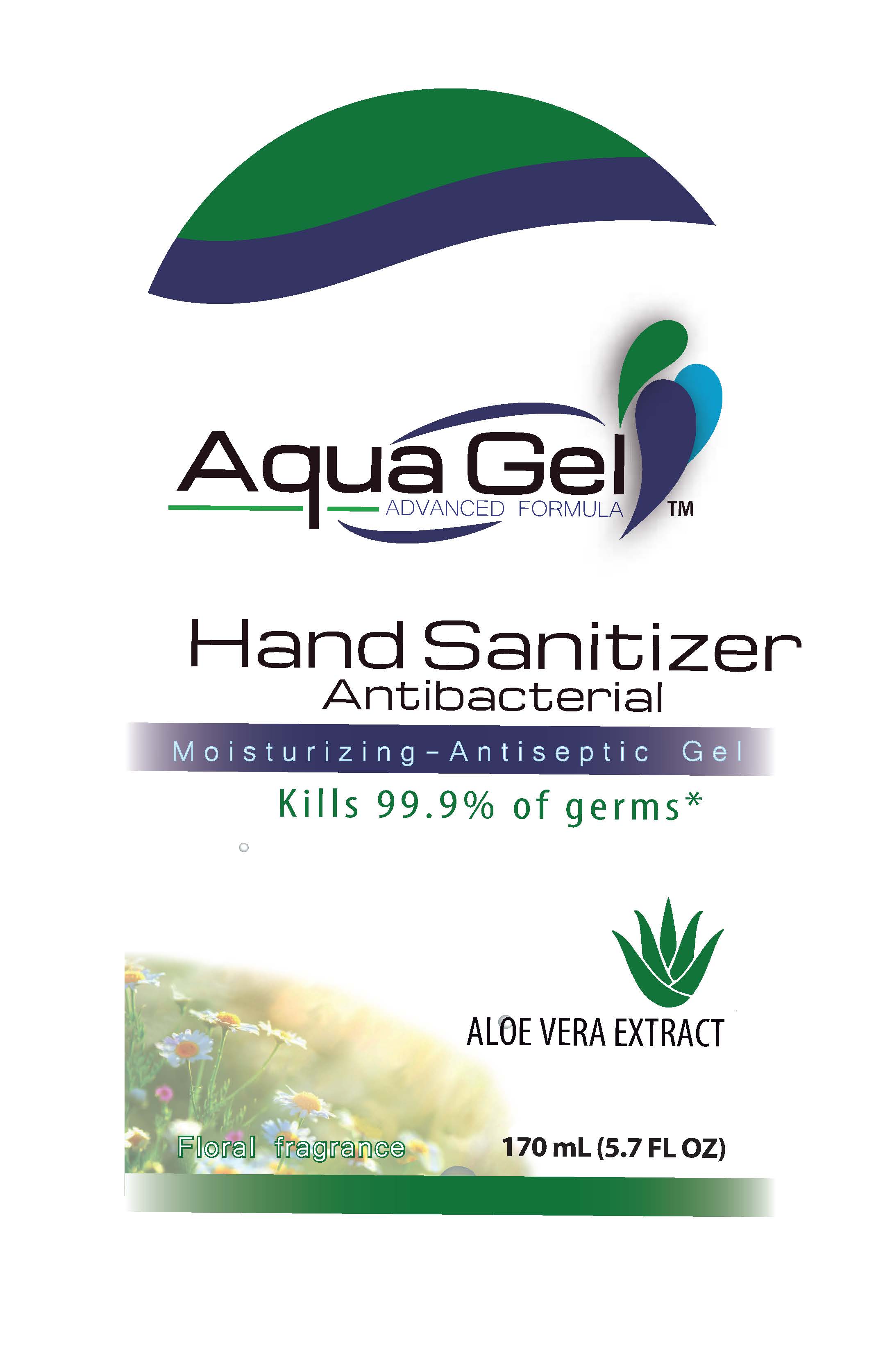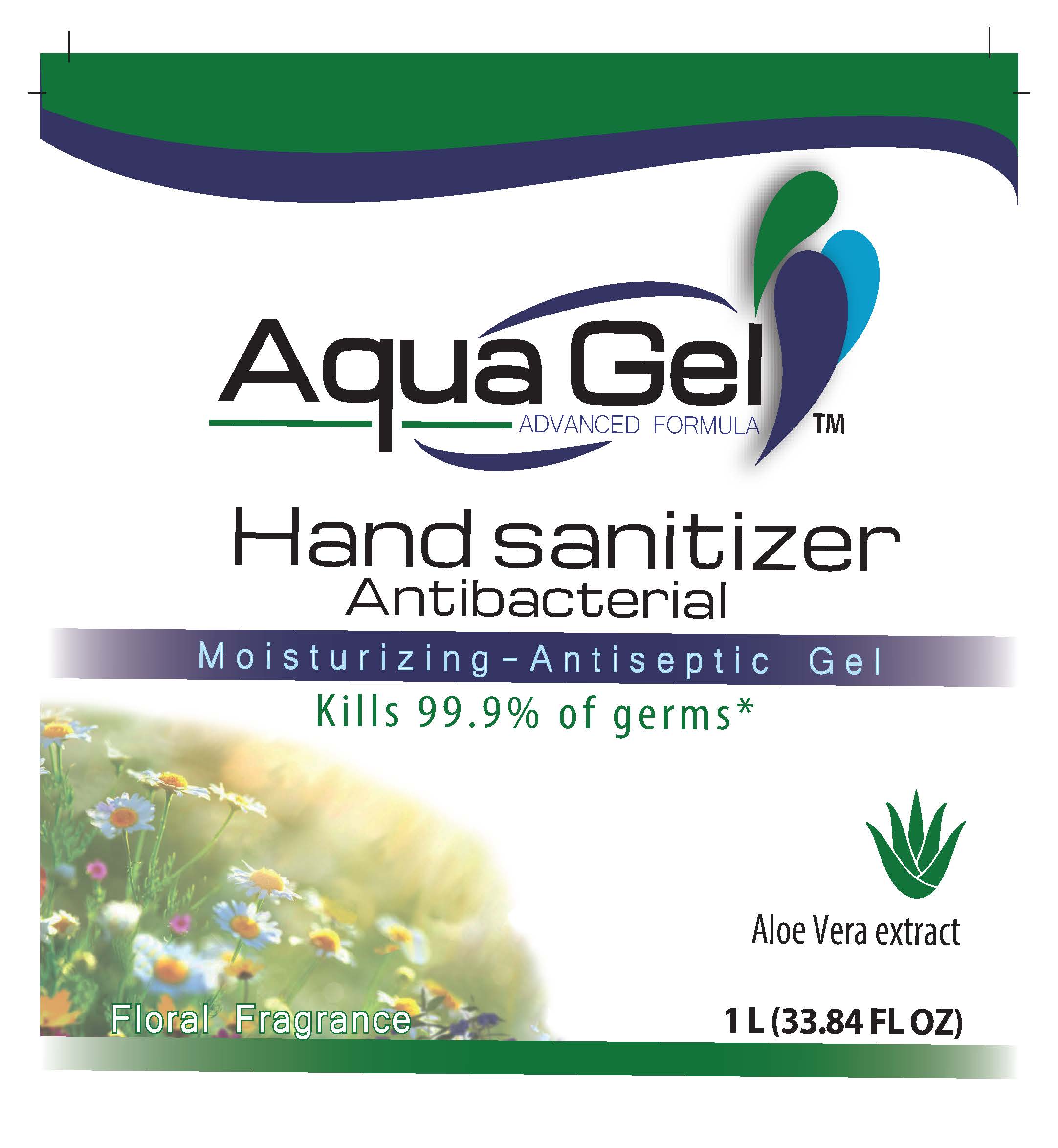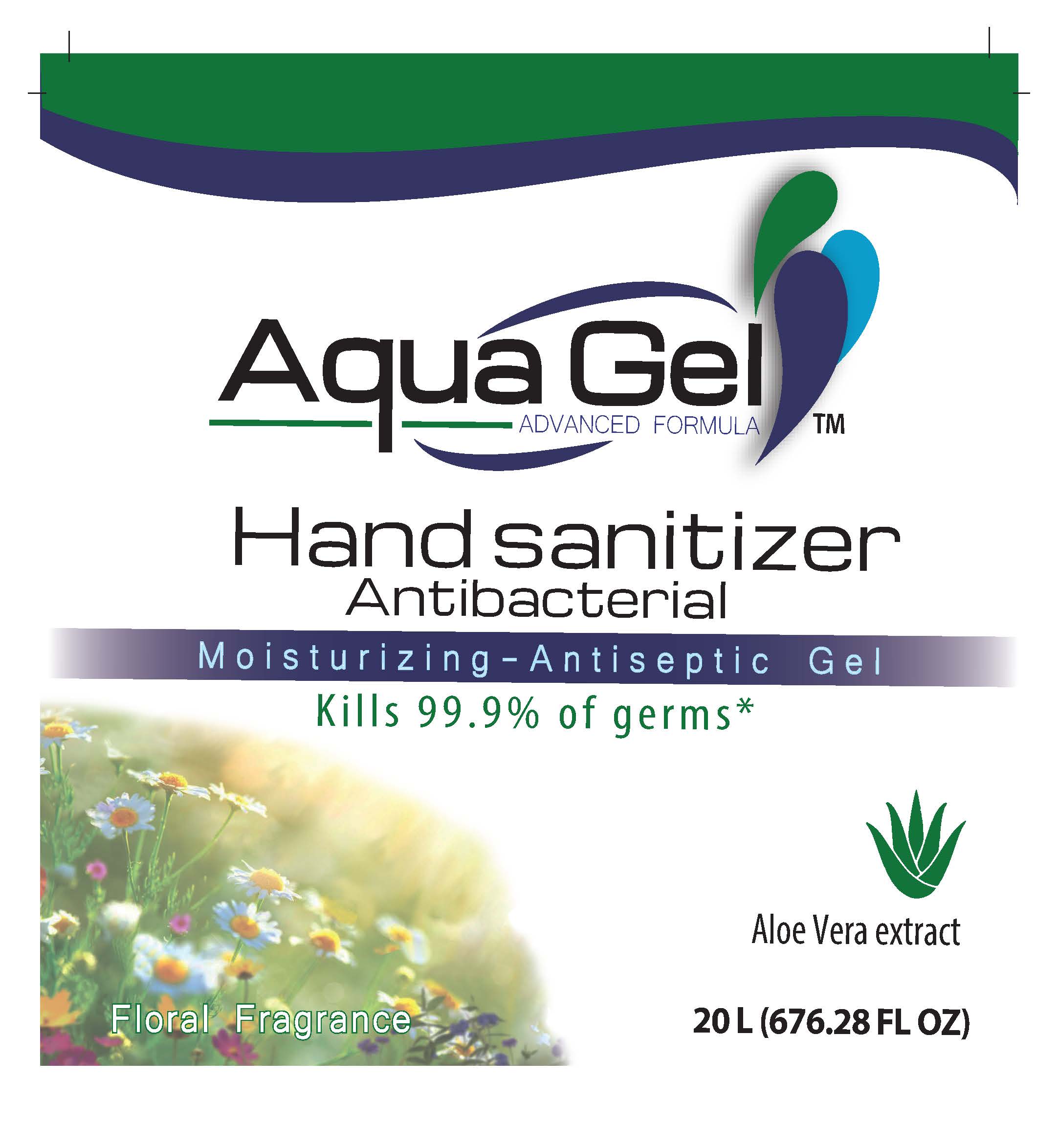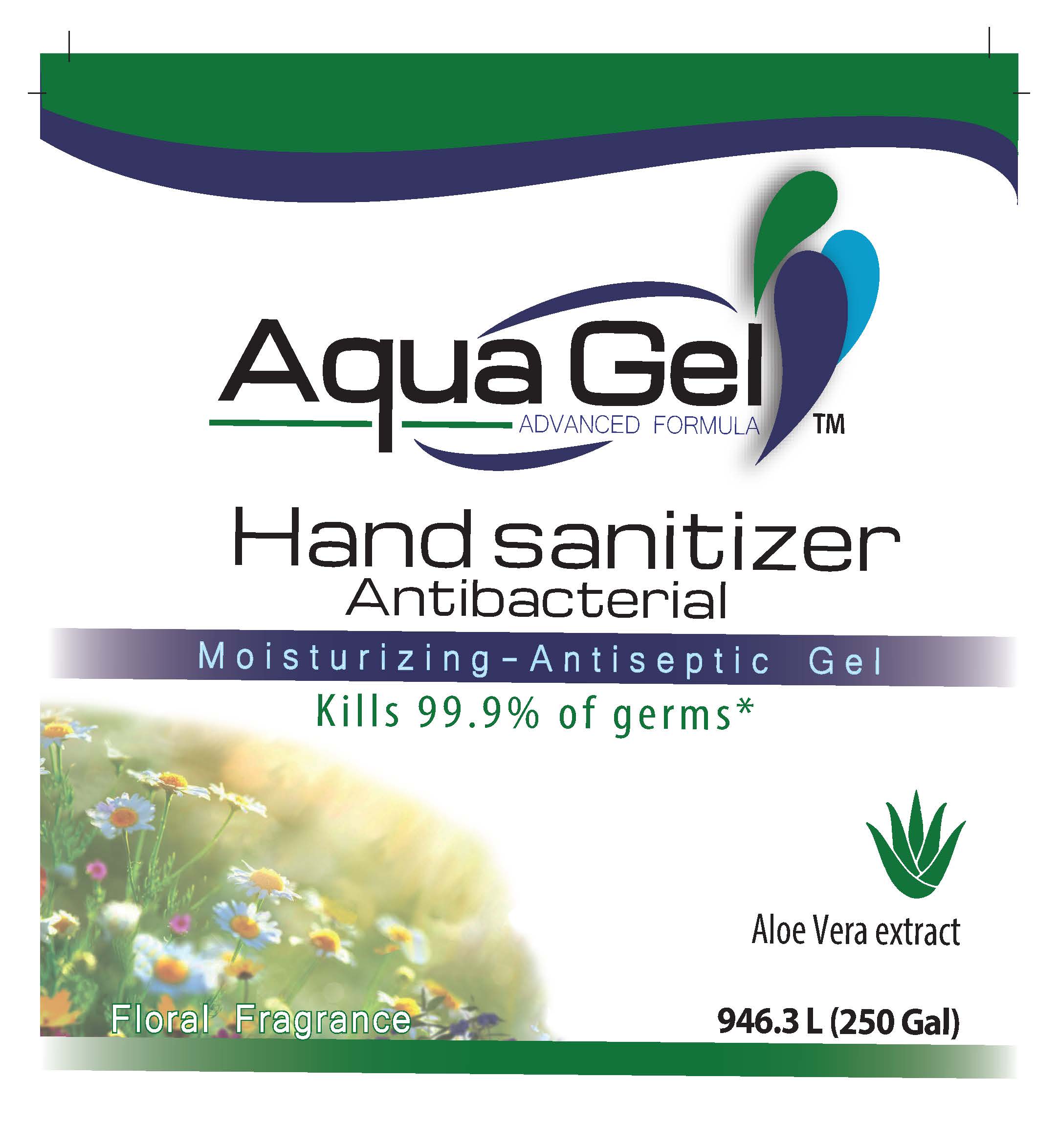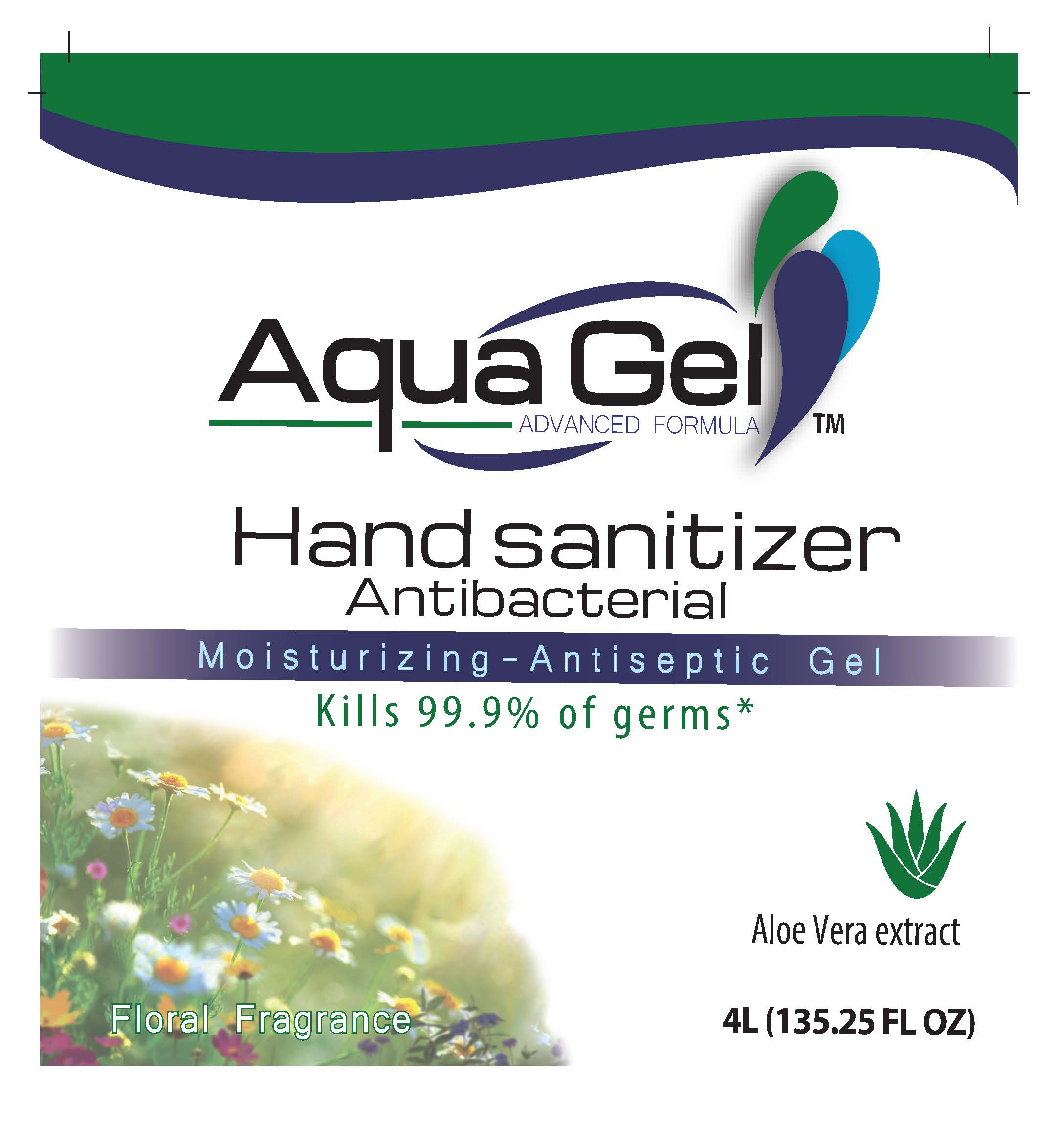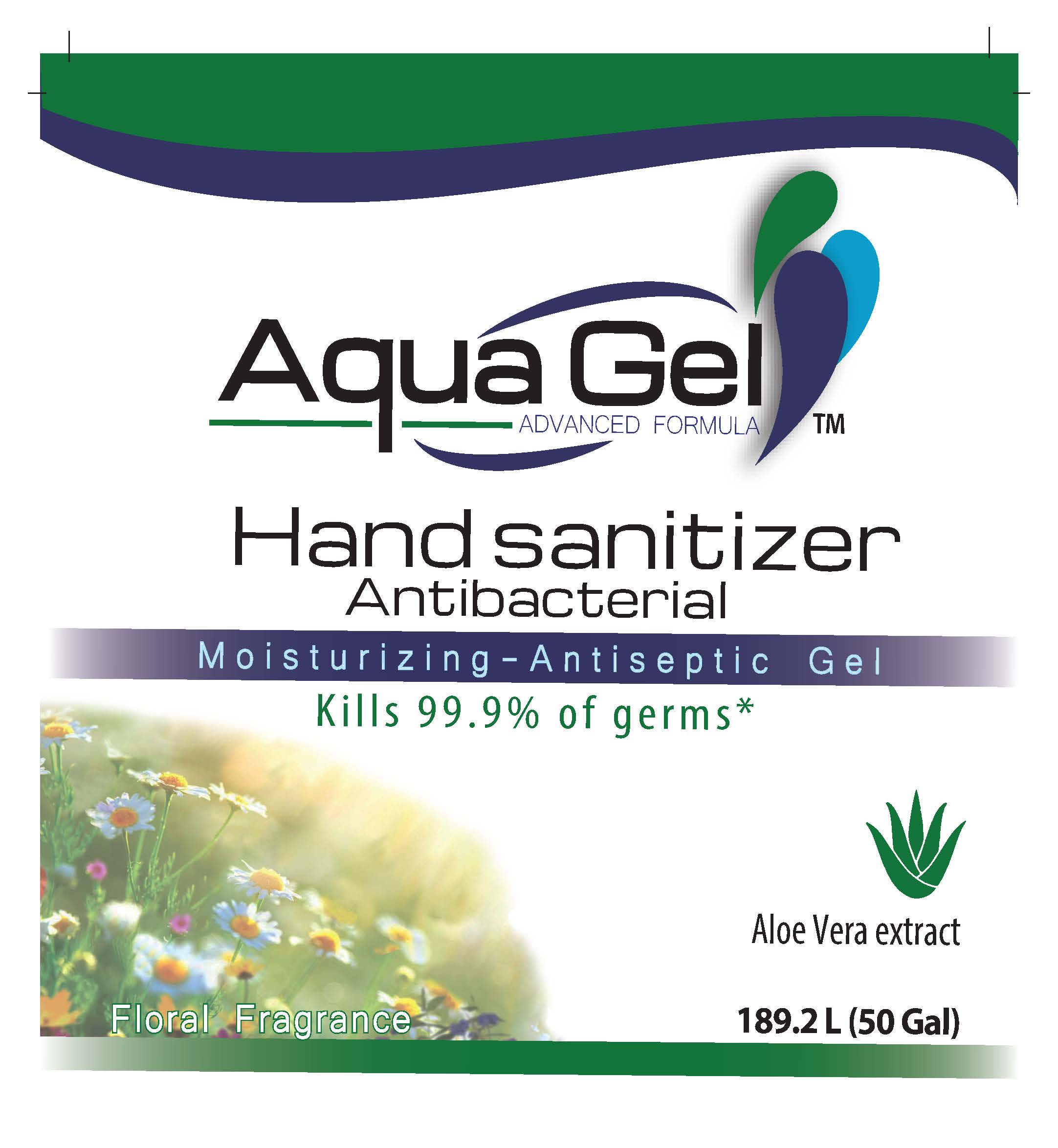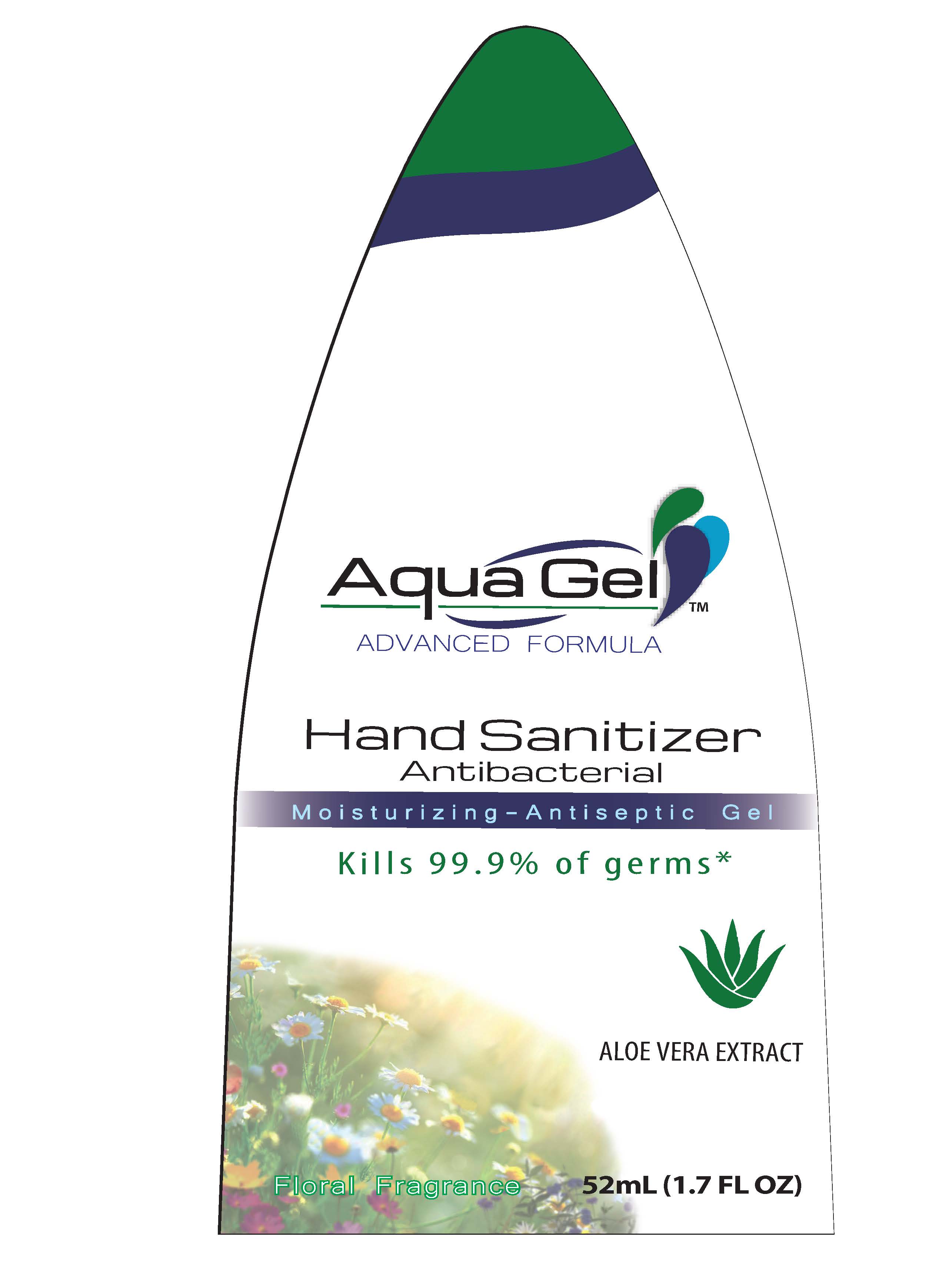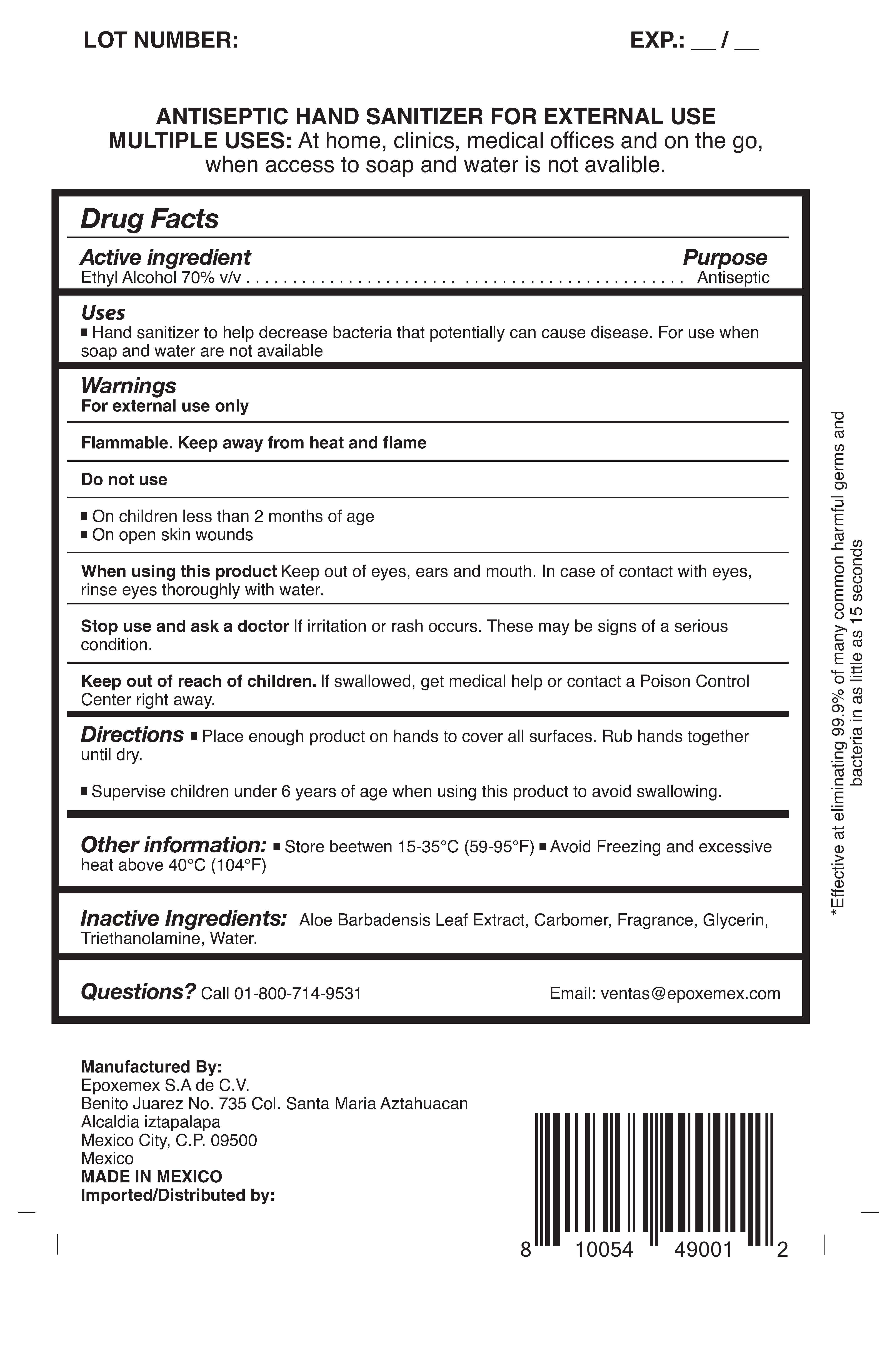 DRUG LABEL: AquaGel Advanced Formula Hand Sanitizer
NDC: 79996-050 | Form: GEL
Manufacturer: EPOXEMEX, S.A. de C.V.
Category: otc | Type: HUMAN OTC DRUG LABEL
Date: 20200917

ACTIVE INGREDIENTS: ALCOHOL 70 mL/100 mL
INACTIVE INGREDIENTS: GLYCERIN; ALOE; WATER; CARBOMER 934; TRIETHANOLAMINE HYDRIODIDE

Active Ingredient(s)

Ethyl Alcohol 70% v/v. Purpose: Antiseptic

Purpose

Antiseptic, Hand Sanitizer

Use

Hand Sanitizer to help reduce bacteria that potentially can cause disease. For use when soap and water are not available.

Warnings

For external use only. Flammable. Keep away from heat or flame

Do not use

- in children less than 2 months of age
- on open skin wounds

When using this product keep out of eyes, ears, and mouth. In case of contact with eyes, rinse eyes thoroughly with water.
Stop use and ask a doctor if irritation or rash occurs. These may be signs of a serious condition.
Keep out of reach of children. If swallowed, get medical help or contact a Poison Control Center right away.

Stop use and ask a doctor if irritation or rash occurs. These may be signs of a serious condition.

Keep out of reach of children. If swallowed, get medical help or contact a Poison Control Center right away.

Directions

- Place enough product on hands to cover all surfaces. Rub hands together until dry.
- Supervise children under 6 years of age when using this product to avoid swallowing.

Other information

- Store between 15-30C (59-86F)
- Avoid freezing and excessive heat above 40C (104F)

Inactive ingredients

water, aloe extract, Carbomer, Fragrance,glycerin, Triethanolamine

Package Label - Principal Display Panel

20L NDC:79996-050-07

1L NDC:79996-050-03

4L NDC:79996-050-02

52 mL NDC:79996-050-04

170 mL NDC:79996-050-01

50 Gallon NDC:79996-050-06 250 Gallon NDC:79996-050-05

Back Label for NDC:79996-050-01,79996-050-02,79996-050-03,79996-050-04,79996-050-05,79996-050-06,79996-050-07

,